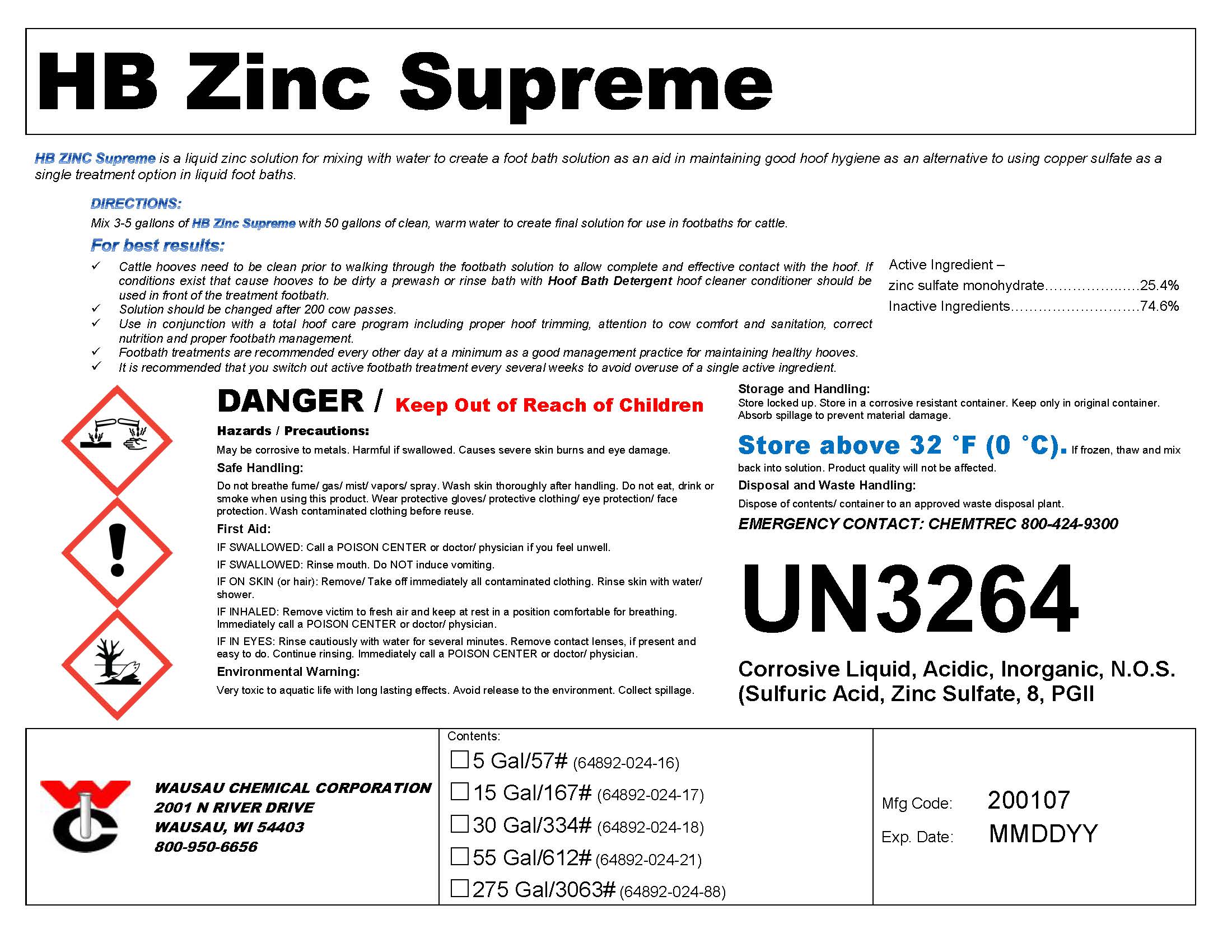 DRUG LABEL: HB Zinc Supreme
NDC: 64892-024 | Form: SOLUTION
Manufacturer: Wausau Chemical
Category: animal | Type: OTC ANIMAL DRUG LABEL
Date: 20200107

ACTIVE INGREDIENTS: ZINC SULFATE MONOHYDRATE 339.1 g/1 L

HB ZincSupreme
Liquid Zinc Hoof Bath Solution

DISPOSAL AND WASTE HANDLING

Dispose of contents/container to an approved waste disposal plant.

ENVIRONMENTAL WARNING

Very toxic to aquatic life with long lasting effects. Avoid release to the environment. Collect spillage.

GENERAL PRECAUTIONS

DANGER / Keep Out of Reach of Children

First Aid:

IF SWALLOWED: Call a POISON CENTER or doctor/ physician if you feel unwell.
IF SWALLOWED: Rinse mouth. Do NOT induce vomiting.
IF ON SKIN (or hair): Remove/ Take off immediately all contaminated clothing. Rinse skin with water/ shower.
IF INHALED: Remove victim to fresh air and keep at rest in a position comfortable for breathing. Immediately call a POISON CENTER or doctor/ physician.
IF IN EYES: Rinse cautiously with water for several minutes. Remove contact lenses, if present and easy to do. Continue rinsing. Immediately call a POISON CENTER or doctor/ physician.

SAFE HANDLING WARNING

Do not breathe fume/ gas/ mist/ vapors/ spray. Wash skin thoroughly after handling. Do not eat, drink or smoke when using this product. Wear protective gloves/ protective clothing/ eye protection/ face protection. Wash contaminated clothing before reuse.

STORAGE AND HANDLING

Store locked up. Store in a corrosive resistant container. Keep only in original container. Absorb spillage to prevent material-damage.
Store above 32 °F (0 °C). If frozen, thaw and mix back into solution. Product quality will not be affected.

DIRECTIONS:
Mix 3-5 gallons of HB Zinc Supreme with 50 gallons of clean, warm water to create final solution for use in footbaths for cattle.

For best results:
Cattle hooves need to be clean prior to walking through the footbath solution to allow complete and effective contact with the hoof. If conditions exist that cause hooves to be dirty a prewash or rinse bath with Hoof Bath Detergent hoof cleaner conditioner should be used in front of the treatment footbath.

Solution should be changed after 200 cow passes.

Use in conjunction with a total hoof care program including proper hoof trimming, attention to cow comfort and sanitation, correct nutrition and proper footbath management.

Footbath treatments are recommended every other day at a minimum as a good management practice for maintaining healthy hooves.

 It is recommended that you switch out active footbath treatment every several weeks to avoid overuse of a single active ingredient.

Active Ingredient – zinc sulfate monohydrate......................................................................25.4%

Wausau Chemical Corporation

2001 N River Drive

Wausau, WI 54403

800-950-6656